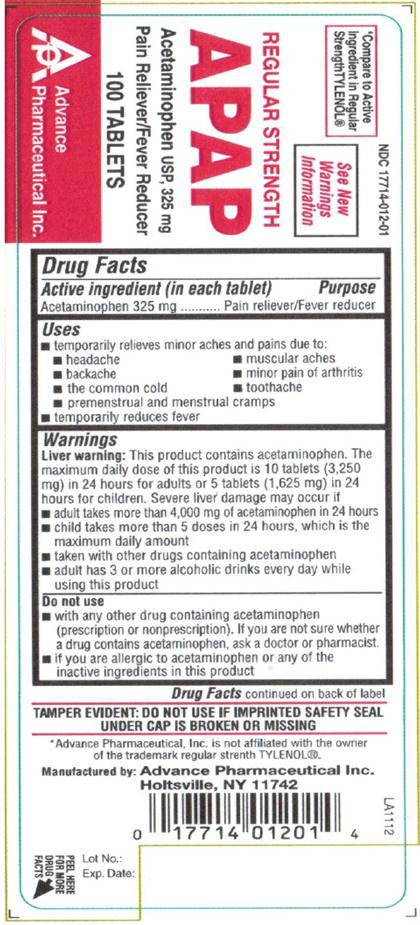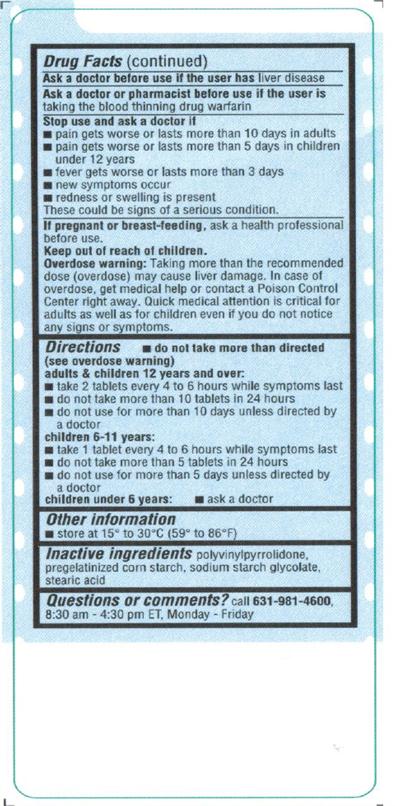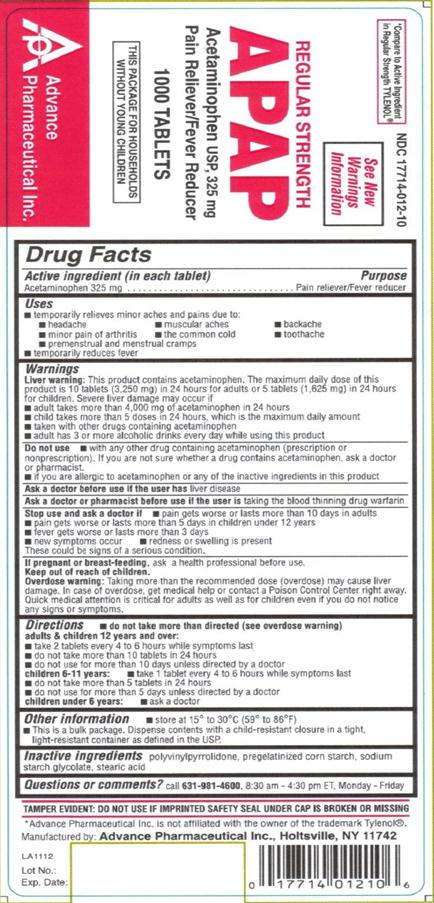 DRUG LABEL: Acetaminophen
NDC: 17714-012 | Form: TABLET
Manufacturer: Advance Pharmaceutical Inc.
Category: otc | Type: HUMAN OTC DRUG LABEL
Date: 20171222

ACTIVE INGREDIENTS: ACETAMINOPHEN 325 mg/1 1
INACTIVE INGREDIENTS: POVIDONE; STARCH, CORN; SODIUM STARCH GLYCOLATE TYPE A POTATO; STEARIC ACID

ACETAMINOPHEN 325 mg

Active Ingredient

(in each tablet)

Acetaminophen 325 mg

Purpose

Pain Reliever / Fever Reducer

Uses

temporarily reduces fever and relieves minor aches and pains caused by

- common cold
- headache
- toothache
- muscular aches
- premenstrual and menstrual cramps

Warnings

Liver warning: this product contains acetaminophen. Severe liver damage may occur if

- adult takes more than 12 tablets in 24 hours, which is the maximum daily amount
- child takes more than 5 tablets in 24 hours, which is the maximum daily amount
- taken with other drugs containing acetaminophen
- adult has 3 or more alcoholic drinks every day while using this product

do not use with any other drug containing acetaminophen (prescription or non prescription). If you are not sure whether a drug contains acetaminophen, ask a doctor or pharmacist.

Ask a doctor before use if the user has liver disease

Ask a doctor or pharmacist before use if the user is taking the blood thinning drug warfarin

Stop use and ask a doctor if

- adult’s pain gets worse or lasts more than 10 days
- child’s pain gets worse or lasts more than 5 days
- fever gets worse or lasts more than 3 days
- redness or swelling is present
- any new symptoms appear

If pregnant or breast-feeding, ask a health professional before use.

Keep out of reach of children.

In case of overdose, get medical help or contact a Poison Control Center right away. Prompt medical attention is critical for adults as well as for children, even if you do not notice any signs or symptoms.

Directions

adults and children 12 years and over | 1-2 tablets every 4 hours or 2-3 tablets every 6 hours while symptoms last, not more than 12 tablets in 24 hours
children 6 to 11 years | 1 tablet every 4 hours while symptoms last, not more than 5 tablets in 24 hours
children under 6 years | ask a doctor

Other Information

- store at 15-30 °C (59-86 °F)

For Bulk package: This is a bulk package, dispense contents with a child-resistant closure in a tight, light resistant container as defined in the USP.

Inactive Ingredients

polyvinylpyrrolidone, pregelatinized corn starch, sodium starch glycolate, stearic acid

Questions or Comments

TAMPER EVIDENT: DO NOT USE IF IMPRINTED SAFETY SEAL UNDER CAP IS BROKEN OR MISSING

Manufactured by: Advance Pharmaceutical, Inc. Holtsville, NY 11742

PACKAGE LABEL.PRINCIPAL DISPLAY PANEL

NDC: 17714-012-01 – 100 COUNT

NDC: 17714-012-10 – 1000 COUNT